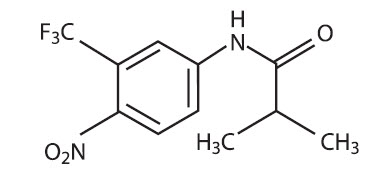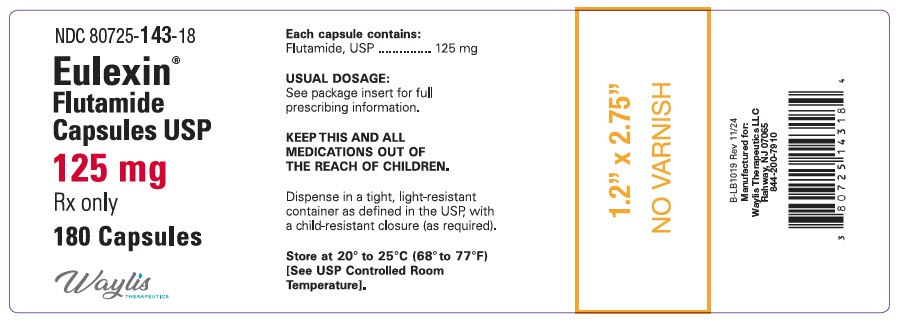 DRUG LABEL: Eulexin
NDC: 80725-143 | Form: CAPSULE
Manufacturer: Waylis Therapeutics LLC
Category: prescription | Type: HUMAN PRESCRIPTION DRUG LABEL
Date: 20250204

ACTIVE INGREDIENTS: flutamide 125 mg/1 1

EULEXIN® (flutamide) CAPSULES USP

Rx Only

WARNINGS

Hepatic Injury

There have been postmarketing reports of hospitalization and rarely death due to liver failure in patients taking Eulexin® . Evidence of hepatic injury included elevated serum transaminase levels, jaundice, hepatic encephalopathy and death related to acute hepatic failure. The hepatic injury was reversible after discontinuation of therapy in some patients. Approximately half of the reported cases occurred within the initial 3 months of treatment with Eulexin®.

Serum transaminase levels should be measured prior to starting treatment with Eulexin®. Eulexin® is not recommended in patients whose ALT values exceed twice the upper limit of normal. Serum transaminase levels should then be measured monthly for the first 4 months of therapy, and periodically thereafter. Liver function tests also should be obtained at the first signs and symptoms suggestive of liver dysfunction, e.g., nausea, vomiting, abdominal pain, fatigue, anorexia, "flu-like" symptoms, hyperbilirubinuria, jaundice or right upper quadrant tenderness. If at any time, a patient has jaundice, or their ALT rises above 2 times the upper limit of normal, Eulexin® should be immediately discontinued with close follow-up of liver function tests until resolution.

DESCRIPTION

Eulexin® capsules contain flutamide, an acetanilid, nonsteroidal, orally active antiandrogen having the chemical name, α,α,α-trifluoro-2-methyl-4'-nitro-m-propionotoluidide.

Each capsule contains 125 mg flutamide. The compound is a buff to yellow powder with a molecular weight of 276.22 and the following structural formula:

C11H11F3N2O3

In addition, each capsule contains the following inactive ingredients: corn starch, lactose monohydrate, magnesium stearate, povidone, and sodium lauryl sulfate. Gelatin capsule shells may contain gelatin, silicon dioxide, sodium lauryl sulfate, titanium dioxide, FDA/E172 Red Iron Oxide, FDA/E172 Yellow Iron Oxide, and black ink containing pharmaceutical glaze (modified) in SD-45, synthetic black iron oxide, N-butyl alcohol, SDA-3A alcohol, FD&C Blue No.2 Aluminum Lake, FD&C Red No.40 Aluminum Lake, FD&C Blue No.1 Aluminum Lake, and D&C Yellow No.10 Aluminum Lake.

CLINICAL PHARMACOLOGY

General

In animal studies, flutamide demonstrates potent antiandrogenic effects. It exerts its antiandrogenic action by inhibiting androgen uptake and/or by inhibiting nuclear binding of androgen in target tissues or both. Prostatic carcinoma is known to be androgen-sensitive and responds to treatment that counteracts the effect of androgen and/or removes the source of androgen, e.g., castration. Elevations of plasma testosterone and estradiol levels have been noted following flutamide administration.

Pharmacokinetics

Absorption

Analysis of plasma, urine, and feces following a single oral 200 mg dose of tritium-labeled Eulexin® to human volunteers showed that the drug is rapidly and completely absorbed. Following a single 250 mg oral dose to normal adult volunteers, the biologically active alpha-hydroxylated metabolite reaches maximum plasma concentrations in about 2 hours, indicating that it is rapidly formed from flutamide. Food has no effect on the bioavailability of flutamide.

Distribution

In male rats administered an oral 5 mg/kg dose of ^14C-flutamide neither flutamide nor any of its metabolites is preferentially accumulated in any tissue except the prostate. Total drug levels were highest 6 hours after drug administration in all tissues. Levels declined at roughly similar rates to low levels at 18 hours. The major metabolite was present at higher concentrations than Eulexin® in all tissues studied. Following a single 250 mg oral dose to normal adult volunteers, low plasma concentrations of Eulexin® were detected. The plasma half-life for the alpha-hydroxylated metabolite of Eulexin® is approximately 6 hours. Eulexin®, in vivo, at steady-state plasma concentrations of 24 to 78 ng/mL, is 94% to 96% bound to plasma proteins. The active metabolite of Eulexin® , in vivo, at steady-state plasma concentrations of 1556 to 2284 ng/mL, is 92% to 94% bound to plasma proteins.

Metabolism

The composition of plasma radioactivity, following a single 200 mg oral dose of tritium-labeled Eulexin® to normal adult volunteers, showed that Eulexin® is rapidly and extensively metabolized, with Eulexin® comprising only 2.5% of plasma radioactivity 1 hour after administration. At least six metabolites have been identified in plasma. The major plasma metabolite is a biologically active alpha-hydroxylated derivative which accounts for 23% of the plasma tritium 1 hour after drug administration. The major urinary metabolite is 2-amino-5nitro-4-(trifluoromethyl)phenol.

Excretion

Eulexin® and its metabolites are excreted mainly in the urine with only 4.2% of a single dose excreted in the feces over 72 hours.

Plasma Pharmacokinetics of flutamide and Hydroxyflutamide in Geriatric Volunteers (mean ± SD)
 | Single Dose flutamide | Hydroxyflutamide | Steady-State flutamide | Hydroxyflutamide
Cmax (ng/mL) | 25.2 ± 34.2 | 894 ± 406 | 113 ± 213 | 1629 ± 586
Elimination half-life (hr) | — | 8.1 ± 1.3 | 7.8 | 9.6 ± 2.5
Tmax (hr) | 1.9 ± 0.7 | 2.7 ± 1.0 | 1.3 ± 0.7 | 1.9 ± 0.6
Cmin (ng/mL) | — | — | — | 673 ± 316

Special Populations

Geriatric

Following multiple oral dosing of 250 mg t.i.d. in normal geriatric volunteers, Eulexin® and its active metabolite approached steady-state plasma levels (based on pharmacokinetic simulations) after the fourth Eulexin® dose. The half-life of the active metabolite in geriatric volunteers after a single Eulexin® dose is about 8 hours and at steady-state in 9.6 hours.

Race

There are no known alterations in Eulexin® absorption, distribution, metabolism, or excretion due to race.

Renal Impairment

Following a single 250 mg dose of Eulexin® administered to subjects with chronic renal insufficiency, there appeared to be no correlation between creatinine clearance and either Cmax or AUC of Eulexin®. Renal impairment did not have an effect on the Cmax or AUC of the biologically active alpha- hydroxylated metabolite of Eulexin®. In subjects with creatinine clearance of < 29 mL/min, the half-life of the active metabolite was slightly prolonged. Eulexin® and its active metabolite were not well dialyzed. Dose adjustment in patients with chronic renal insufficiency is not warranted.

Hepatic Impairment

No information on the pharmacokinetics of Eulexin® in hepatic impairment is available (see BOXED WARNINGS, Hepatic Injury).

Women, Pediatrics

Eulexin® has not been studied in women or pediatric subjects.

Drug-Drug Interactions

Interactions between Eulexin® capsules and LHRH-agonists have not occurred. Increases in prothrombin time have been noted in patients receiving warfarin therapy (see PRECAUTIONS).

CLINICAL STUDIES

Eulexin® has been demonstrated to interfere with testosterone at the cellular level. This can complement medical castration achieved with LHRH-agonists which suppresses testicular androgen production by inhibiting luteinizing hormone secretion.

The effects of combination therapy have been evaluated in two studies. One study evaluated the effects of Eulexin® and an LHRH-agonist as neoadjuvant therapy to radiation in stage B2-C prostatic carcinoma and the other study evaluated Eulexin® and an LHRH-agonist as the sole therapy in stage D2 prostatic carcinoma.

Stage B2-C Prostatic Carcinoma

The effects of hormonal treatment combined with radiation was studied in 466 patients (231 Eulexin® capsules + goserelin acetate implant + radiation, 235 radiation alone) with bulky primary tumors confined to the prostate (stage B2) or extending beyond the capsule (stage C), with or without pelvic node involvement.

In this multicentered, controlled trial, administration of Eulexin® capsules (250 mg t.i.d.) and goserelin acetate (3.6 mg depot) prior to and during radiation was associated with a significantly lower rate of local failure compared to radiation alone (16% vs. 33% at 4 years, P < 0.001). The combination therapy also resulted in a trend toward reduction in the incidence of distant metastases (27% vs. 36% at 4 years, P = 0.058). Median disease-free survival was significantly increased in patients who received complete hormonal therapy combined with radiation as compared to those patients who received radiation alone (4.4 vs 2.6 years, P < 0.001). Inclusion of normal PSA level as a criterion for disease-free survival also resulted in significantly increased median disease-free survival in patients receiving the combination therapy (2.7 vs. 1.5 years, P < 0.001).

Stage D2 Prostatic Carcinoma

To study the effects of combination therapy in metastatic disease, 617 patients (311 leuprolide + Eulexin®, 306 leuprolide + placebo) with previously untreated advanced prostatic carcinoma were enrolled in a large multicentered, controlled clinical trial.

Three and one-half years after the study was initiated, median survival had been reached. The median actuarial survival time was 34.9 months for patients treated with leuprolide and Eulexin® versus 27.9 months for patients treated with leuprolide alone. This 7 month increment represents a 25% improvement in overall survival time with the Eulexin® therapy. Analysis of progression-free survival showed a 2.6 month improvement in patients who received leuprolide plus Eulexin®, a 19% increment over leuprolide and placebo.

INDICATIONS AND USAGE

Eulexin® capsules are indicated for use in combination with LHRH-agonists for the management of locally confined Stage B2-C and Stage D2 metastatic carcinoma of the prostate.

Stage B2-C Prostatic Carcinoma

Treatment with Eulexin® capsules and the goserelin acetate implant should start eight weeks prior to initiating radiation therapy and continue during radiation therapy.

Stage D2 Metastatic Carcinoma

To achieve benefit from treatment, Eulexin® capsules should be initiated with the LHRH-agonist and continued until progression.

CONTRAINDICATIONS

Eulexin® capsules are contraindicated in patients who are hypersensitive to Eulexin® or any component of this preparation.

Eulexin® capsules are contraindicated in patients with severe hepatic impairment (baseline hepatic enzymes should be evaluated prior to treatment).

WARNINGS

Hepatic Injury

SEE BOXED WARNINGS

Use in Women

Eulexin® capsules are for use only in men. This product has no indication for women and should not be used in this population, particularly for nonserious or nonlife-threatening conditions.

Fetal toxicity

Eulexin® may cause fetal harm when administered to a pregnant woman (see Pregnancy).

Aniline toxicity

One metabolite of Eulexin® is 4-nitro-3-fluoro-methylaniline. Several toxicities consistent with aniline exposure, including methemoglobinemia, hemolytic anemia and cholestatic jaundice have been observed in both animals and humans after Eulexin® administration. In patients susceptible to aniline toxicity (e.g. persons with glucose-6-phosphate dehydrogenase deficiency, hemoglobin M disease and smokers), monitoring of methemoglobin levels should be considered.

PRECAUTIONS

General

In clinical trials, gynecomastia occurred in 9% of patients receiving Eulexin® together with medical castration.

Information for Patients

Patients should be informed that Eulexin® capsules and the drug used for medical castration should be administered concomitantly, and that they should not interrupt their dosing or stop taking these medications without consulting their physician.

Laboratory Tests

Regular assessment of serum Prostate Specific Antigen (PSA) may be helpful in monitoring the patient's response. If PSA levels rise significantly and consistently during Eulexin® therapy the patient should be evaluated for clinical progression. For patients who have objective progression of disease together with an elevated PSA, a treatment period free of antiandrogen while continuing the LHRH analogue may be considered.

Drug Interactions

Increases in prothrombin time have been noted in patients receiving long-term warfarin therapy after Eulexin® was initiated. Therefore close monitoring of prothrombin time is recommended and adjustment of the anticoagulant dose may be necessary when Eulexin® capsules are administered concomitantly with warfarin.

Carcinogenesis and Mutagenesis and Impairment of Fertility

In a 1 year dietary study in male rats, interstitial cell adenomas of the testes were present in 49% to 75% of all treated rats (daily doses of 10, 30, and 50 mg/kg/day were administered). These produced plasma Cmax values that are 1, 2, 3, and 4 fold respectively, those associated with therapeutic doses in humans. In male rats similarly dosed for 1 year, tumors were still present after 1 year of a drug-free period, but the incidences were 43% to 47%. In a 2 year carcinogenicity study in male rats, daily administration of Eulexin® at t hese same doses produced testicular interstitial cell adenomas in 91% to 95% of all treated rats as opposed to 11% of untreated control rats. Mammary adenomas, adenocarcinomas, and fibroadenomas were increased in treated male rats at exposure levels that were 1 to 4 fold those observed during therapeutic dosing in humans. There are likewise reports of malignant breast neoplasms in men treated with Eulexin® capsules (see ADVERSE REACTIONS section).

Eulexin® did not demonstrate DNA modifying activity in the Ames Salmonella/microsome Mutagenesis Assay. Dominant lethal tests in rats were negative. Reduced sperm counts were observed during a 6 week study of Eulexin® monotherapy in normal human volunteers.

Eulexin® did not affect estrous cycles or interfere with the mating behavior of male and female rats when the drug was administered at 25 and 75 mg/kg/day prior to mating. Males treated with 150 mg/kg/day (30 times the minimum effective antiandrogenic dose) failed to mate; mating behavior returned to normal after dosing was stopped. Conception rates were decreased in all dosing groups. Suppression of spermatogenesis was observed in rats dosed for 52 weeks at approximately 3, 8, or 17 times the human dose and in dogs dosed for 78 weeks at 1.4, 2.3, and 3.7 times the human dose.

Animal Toxicology

Serious cardiac lesions were observed in 2/10 beagle dogs receiving 25 mg/kg/day for 78 weeks and 3/16 receiving 40 mg/kg/day for 2 to 4 years. These lesions, indicative of chronic injury and repair processes, included chronic myxomatous degeneration, intra-atrial fibrosis, myocardial acidophilic degeneration, vasculitis and perivasculitis. The doses at which these lesions occurred were associated with 2-hydroxyflutamide levels that were 1 to 12 fold greater than those observed in humans at therapeutic levels.

Pregnancy

Pregnancy Category D

There was decreased 24 hour survival in the offspring of pregnant rats treated with Eulexin® at doses of 30, 100 or 200 mg/kg/day (approximately 3, 9 and 19 times the human dose). A slight increase in minor variations in the development of the sternebrae and vertebrae was seen in fetuses of rats treated with two higher doses. Feminization of the male rats also occurred at the two higher dose levels. There was a decreased survival rate in the offspring of rabbits receiving the highest dose (15 mg/kg/day, equal to 1.4 times the human dose).

ADVERSE REACTIONS

Stage B2-C Prostatic Carcinoma

Treatment with Eulexin® capsules and the goserelin acetate implant did not add substantially to the toxicity of radiation treatment alone. The following adverse experiences were reported during a multicenter clinical trial comparing Eulexin® + goserelin acetate implant + radiation versus radiation alone. The most frequently reported (greater than 5%) adverse experiences are listed below:

Adverse Events During Acute Radiation Therapy (within first 90 days of radiation therapy)
 | (n=231) Goserelin Acetate Implant + Eulexin® + Radiation | (n=235) Radiation Only
 | % All | % All
Rectum/Large Bowel | 80 | 76
Bladder | 58 | 60
Skin | 37 | 37

Adverse Events During Late Radiation Phase (after 90 days of radiation therapy)
 | (n=231) Goserelin Acetate Implant + Eulexin® + Radiation | (n=235) Radiation Only
 | % All | % All
Diarrhea | 36 | 40
Cystitis | 16 | 16
Rectal Bleeding | 14 | 20
Proctitis | 8 | 8
Hematuria | 7 | 12

Additional adverse event data were collected for the combination therapy with radiation group over both the hormonal treatment and hormonal treatment plus radiation phases of the study. Adverse experiences occurring in more than 5% of patients in this group, over both parts of the study, were hot flashes (46%), diarrhea (40%), nausea (9%), and skin rash (8%).

Stage D2 Metastatic Carcinoma

The following adverse experiences were reported during a multicenter clinical trial comparing Eulexin® + LHRH agonist versus placebo + LHRH agonist.

The most frequently reported (greater than 5%) adverse experiences during treatment with Eulexin® capsules in combination with an LHRH agonist are listed in the table below. For comparison, adverse experiences seen with an LHRH agonist and placebo are also listed in the following table.

 | (n=294) Eulexin® + LHRH agonist | (n=28) Placebo + LHRH agonist
 | % All | % All
Hot Flashes | 61 | 57
Loss of Libido | 36 | 31
Impotence | 33 | 29
Diarrhea | 12 | 4
Nausea/Vomiting | 11 | 10
Gynecomastia | 9 | 11
Other | 7 | 9
Other GI | 6 | 4

As shown in the table, for both treatment groups, the most frequently occurring adverse experiences (hot flashes, impotence, loss of libido) were those known to be associated with low serum androgen levels and known to occur with LHRH agonists alone.

The only notable difference was the higher incidence of diarrhea in the Eulexin® + LHRH agonist group (12%), which was severe in 5% as opposed to the placebo + LHRH agonist (4%), which was severe in less than 1%.

In addition, the following adverse reactions were reported during treatment with Eulexin® + LHRH agonist.

Cardiovascular System: hypertension in 1% of patients.

Central Nervous System: CNS (drowsiness/confusion/depression/anxiety/nervousness) reactions occurred in 1% of patients.

Gastrointestinal System: anorexia 4%, and other GI disorders occurred in 6% of patients.

Hematopoietic System: anemia occurred in 6%, leukopenia in 3%, and thrombocytopenia in 1% of patients.

Liver and Biliary System: hepatitis and jaundice in less than 1% of patients.

Skin: irritation at the injection site and rash occurred in 3% of patients.

Other: edema occurred in 4%, genitourinary and neuromuscular symptoms in 2%, and pulmonary symptoms in less than 1% of patients.

In addition, the following spontaneous adverse experiences have been reported during the marketing of Eulexin® : hemolytic anemia,macrocytic anemia,methemoglobinemia, sulfhemoglobinemia, photosensitivity reactions (including erythema, ulceration, bullous eruptions, and epidermal necrolysis) and urine discoloration. The urine was noted to change to an amber or yellow-green appearance which can be attributed to the Eulexin® and/or its metabolites. Also reported were cholestatic jaundice, hepatic encephalopathy, and hepatic necrosis. The hepatic conditions were often reversible after discontinuing therapy; however, there have been reports of death following severe hepatic injury associated with use of Eulexin®.

Malignant breast neoplasms have occurred rarely in male patients being treated with Eulexin® capsules.

Abnormal Laboratory Test Values: Laboratory abnormalities including elevated SGOT, SGPT, bilirubin values, SGGT, BUN, and serum creatinine have been reported.

OVERDOSAGE

In animal studies with Eulexin® alone, signs of overdose included hypoactivity, piloerection, slow respiration, ataxia, and/or lacrimation, anorexia, tranquilization, emesis, and methemoglobinemia.

Clinical trials have been conducted with Eulexin® in doses up to 1500 mg per day for periods up to 36 weeks with no serious adverse effects reported. Those adverse reactions reported included gynecomastia, breast tenderness, and some increases in SGOT. The single dose of Eulexin® ordinarily associated with symptoms of overdose or considered to be life-threatening has not been established.

Eulexin® is highly protein bound, and is not cleared by hemodialysis. As in the management of overdosage with any drug, it should be borne in mind that multiple agents may have been taken. If vomiting does not occur spontaneously, it should be induced if the patient is alert. General supportive care, including frequent monitoring of the vital signs and close observation of the patient, is indicated.

DOSAGE AND ADMINISTRATION

The recommended dosage is 2 capsules 3 times a day at 8 hour intervals for a total daily dose of 750 mg.

HOW SUPPLIED

Eulexin® capsules USP, 125 mg, are available as opaque, beige/beige capsules, imprinted "w 753" on the cap and body. They are available in bottle of 180 (NDC 80725-143-18).

STORAGE AND HANDLING

Store at 20° to 25°C (68° to 77°F) [See USP Controlled Room Temperature]. Dispense in a tight, light-resistant container as defined in the USP, with a child-resistant closure (as required).

Manufactured for:
Waylis Therapeutics LLC
Wixom, MI 48393

INFORMATION FOR PATIENTS EULEXIN® (FLUTAMIDE) CAPSULES USP RX ONLY

Important information for patients taking Eulexin® capsules.

Read this information carefully each time your prescription is refilled because there may be new information available. This summary does not tell you everything you need to know about Eulexin® therapy. Your doctor is the best source of information about your treatment. Ask your doctor about questions you have.

What is Eulexin® therapy?

Eulexin® capsules, in combination with other therapies, is a treatment option for men with some types of prostate cancer.

Prostate cancer results from the abnormal growth of prostate cells. Medical scientists do not know exactly what causes the abnormal cells, but age, environment, and genetics are important factors. Male hormones ("androgens") cause the cancer to grow. The cancer growth can be slowed down by blocking the effect of androgens.

The Eulexin® product is used together with an injection called "LHRH agonist," as a combined treatment called "total androgen blockade." The goal of this treatment is to reduce androgen levels and to block the effect of androgen on the tumor. The LHRH agonist reduces androgen levels. Eulexin® therapy blocks the effect of androgen on the tumor.

Who should not take the Eulexin® product?

You should not take Eulexin® capsules if you have liver problems or if you are allergic to it. Eulexin® capsules are for use only in men; therefore women should not take Eulexin® capsules.

Are there important risks I should know about Eulexin® therapy?

Some men taking Eulexin® had liver injury and needed to be hospitalized. In rare cases, men died because of liver failure while they were taking Eulexin® capsules. In about half of these cases, the liver failure occurred in the first 3 months that they were taking Eulexin® capsules.

Because the Eulexin® product may cause liver failure, it is very important that you have all blood tests recommended by your doctor. These tests help identify whether you are having liver problems. A recommended schedule for these blood tests is:

- Before starting Eulexin® treatment.
- Every month for the first 4 months of therapy.
- Periodically after the first 4 months.

In addition, you should call your doctor right away if you have any of the following signs or symptoms:

- Loss of appetite.
- Nausea and vomiting.
- Stomach or abdominal pain.
- Fatigue (feeling extremely tired).
- Flu-like symptoms (muscle aches, soreness).
- Brown urine.
- Jaundice (yellowing of the skin or whites of the eyes).

These may be signs of liver failure.

How should I take Eulexin® capsules?

Take your Eulexin® capsules as your doctor has prescribed. The usual dosing is 2 capsules every 8 hours.

Your doctor will determine whether Eulexin® therapy is right for you based on many different factors. These include how large your tumor is, how far it has spread and your physical condition. In addition to Eulexin® capsules, you may be getting other treatments, including regular injections of LHRH agonist or radiation therapy. Do not stop or interrupt any treatment without consulting your healthcare professional.

If you miss a dose of Eulexin® capsules, simply continue therapy with your next scheduled dose. Do not try to make up for it by taking extra capsules.

Can I take other medicines?

If you are taking any other medicines, especially warfarin (a blood-thinning drug), tell your doctor before beginning Eulexin® therapy.

What are the other possible side effects of taking Eulexin® capsules?

In a medical study, when Eulexin® capsules were taken together with an LHRH agonist, the most common side effects were hot flashes, loss of sex drive (libido) and impotence. In addition, some men had diarrhea, nausea or vomiting, and breast enlargement.

In another medical study, when the Eulexin® product was taken together with goserelin acetate (an LHRH agonist) and radiation therapy, the side effects of Eulexin® therapy were about the same as when radiation therapy was given alone. These included hot flashes, diarrhea, nausea and skin rash.

What can I do if I get diarrhea?

If you experience moderate diarrhea due to Eulexin® capsules, the following advice may help:

- drink plenty of fluids
- reduce your intake of dairy products (for example, milk, cheese, yogurt).
- Increase your intake of whole grains, fruits and vegetables.
- Stop laxative use.
- Take nonprescription antidiarrheal medicines.

If your diarrhea continues or it becomes severe, contact your doctor right away.

Are there any other lab tests my doctor will be performing?

Your doctor may perform other regular tests (such as the PSA blood test) to ensure that your body is responding to treatment. Ask your doctor if you have any questions about how your Eulexin® therapy is being monitored.

Please ask your doctor about any questions concerning prostate cancer or Eulexin® therapy, or you can also ask for a more detailed leaflet that is written for healthcare professionals.

Manufactured for:
Waylis Therapeutics LLC
Wixom, MI 48393
844-200-7910

Revised: 01/2024

PRINCIPAL DISPLAY PANEL - 125 mg Capsule Bottle Label

NDC 80725-143-18

Eulexin®
Flutamide
Capsules, USP

125 mg

Rx only

180 Capsules

Waylis
THERAPEUTICS